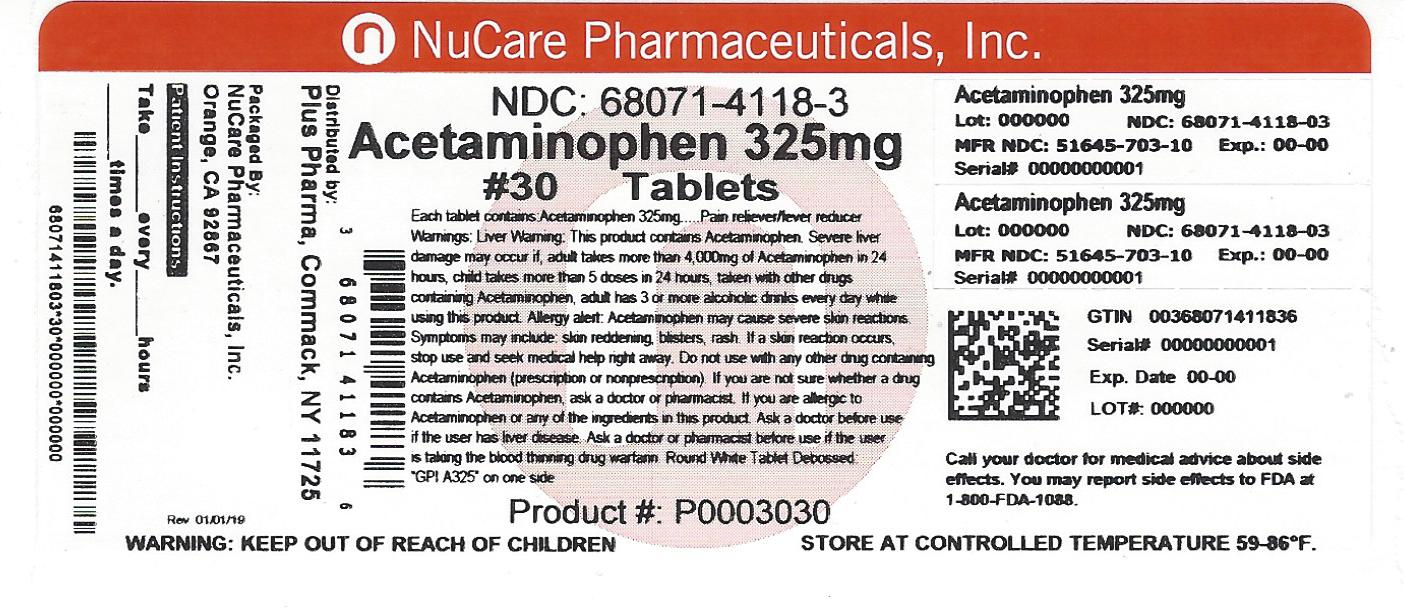 DRUG LABEL: ACETAMINOPHEN
NDC: 68071-4118 | Form: TABLET
Manufacturer: NuCare Pharmaceuticals,Inc.
Category: otc | Type: HUMAN OTC DRUG LABEL
Date: 20220120

ACTIVE INGREDIENTS: ACETAMINOPHEN 325 mg/1 1
INACTIVE INGREDIENTS: POVIDONE; STARCH, CORN; SODIUM STARCH GLYCOLATE TYPE A CORN; STEARIC ACID

Drug Facts

Active ingredient (in each tablet)

Acetaminophen 325 mg

Purposes

Pain reliever/fever reducer

Warnings

Liver warning: This product contains acetaminophen. Severe liver damage may occur if

- adult takes more than 12 tablets in 24 hours, which is the maximum daily amount
- child takes more than 5 doses in 24 hours
- taken with other drugs containing acetaminophen
- adult has 3 or more alcoholic drinks every day while using this product

Allergy alert: acetaminophen may cause severe skin reactions. Symptoms may include:

- skin reddening
- blisters
- rash

If a skin reaction occurs, stop use and seek medical help right away.

Do not use

- with any other drug containing acetaminophen (prescription or non prescription). If you are not sure whether a drug contains acetaminophen, ask a doctor or pharmacist.
- if you are allergic to acetaminophen or any of the inactive ingredients in this product

Ask a doctor before use if the user has

liver disease.

Ask a doctor or pharmacist before use if the user is

taking the blood thinning drug warfarin.

Stop use and ask a doctor if

Pain gets worse or lasts more than 10 days in adults and children

Pain gets worse or lasts more than 5 days in children under 12 years

Fever gets worse or lasts more than 3 days

New symptoms occur

Redness or swelling is present

These could be signs of a serious condition.

PREGNANCY OR BREAST FEEDING

If pregnant or breast-feeding, ask a health professional before use.

Keep out of reach of children.

Overdose warning:

Taking more than the recommended dose (overdose) may cause liver damage. In case of overdose get medical help or contact a Poison Control Center right away. (1-800-222-1222). Quick medical attention is critical for adults as well as for children even if you do not notice any signs or symptoms.

Uses

for the temporary relief of minor aches and pains due to:

- Headache
- Muscular aches
- Backache
- Minor pain of arthritis
- The common cold
- Toothache
- Premenstrual and menstrual cramps

Temporarily reduces fever.

Directions

Do not take more than directed

AGE | DOSE
Adults and Children 12 years and over | - Take 2 tablets every 4 to 6 hours while symptoms last - Do not take more than 12 tablets in 24 hours
Children 6 - 11 years | - Take 1 tablet every 4 to 6 hours while symptoms last - Do not take more than 5 tablets in 24 hours
Children under 6 years | Do not use adult Regular Strength products in children under 6 years of age; this will provide more than the recommended dose (overdose) of acetaminophen and may cause liver damage.

Other information

- Do not use if imprinted Safety Seal under cap is broken or missing
- Store at room temperature

Inactive ingredients

Povidone, Pregelatinized Starch, Sodium Starch Glycolate, Stearic Acid.

Questions?

If you have any questions or comments, or to report an adverse event, please contact (800) 795-9775.